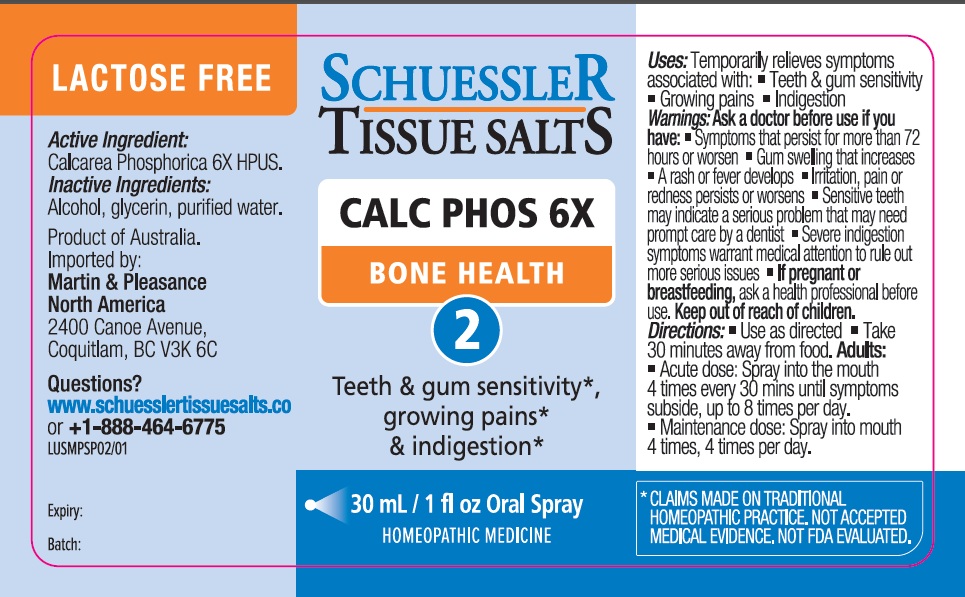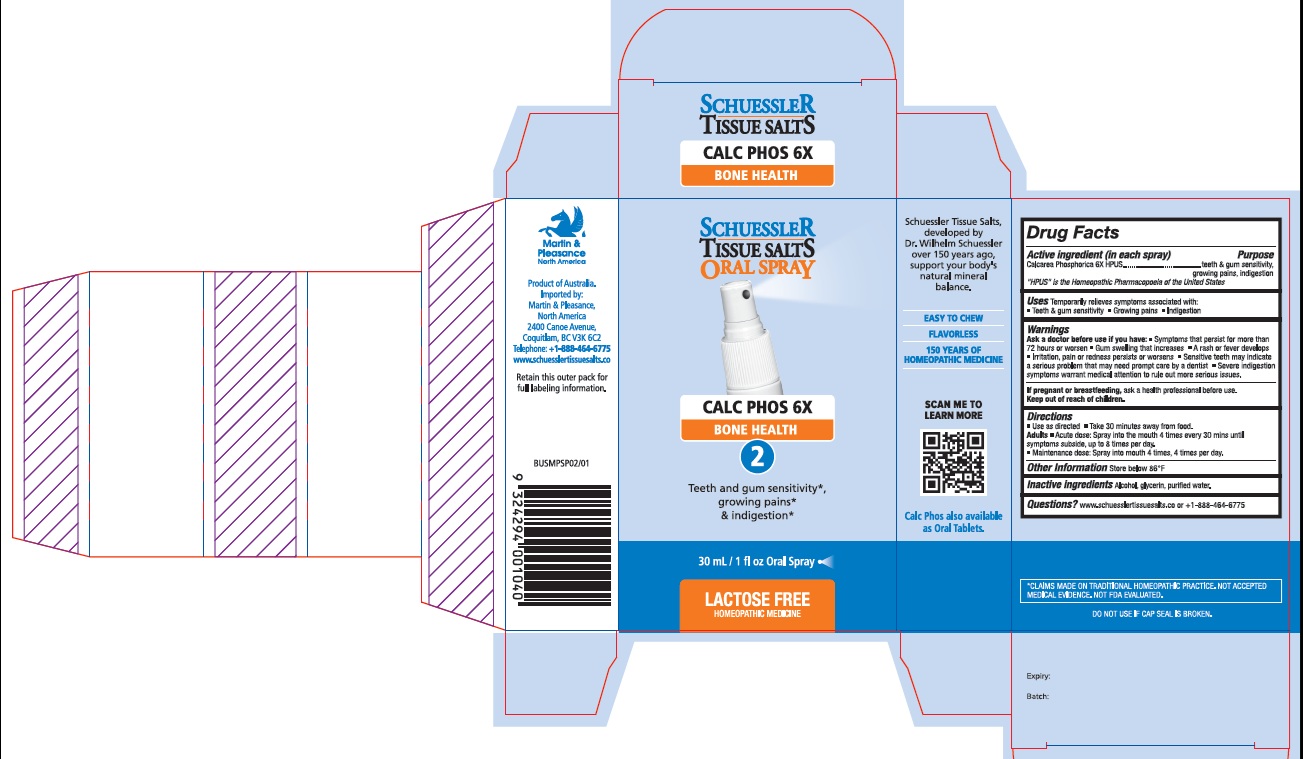 DRUG LABEL: Schuessler Tissue Salts Calc Phos Bone Health 2
NDC: 84999-002 | Form: SPRAY
Manufacturer: Martin & Pleasance Pty Ltd
Category: homeopathic | Type: HUMAN OTC DRUG LABEL
Date: 20250701

ACTIVE INGREDIENTS: ANHYDROUS DIBASIC CALCIUM PHOSPHATE 6 [hp_X]/30 mL
INACTIVE INGREDIENTS: ALCOHOL; GLYCERIN; WATER

Active Ingredients Purpose

Calcarea Phosphorica 6X HPUS teeth & gum sensitivity, growing pains, indigestion

" HPUS" is the Homeopathic Pharmacopoeia of the United States

Uses

Temporarily relieves symptoms associated with:

- Teeth & gum sensitivity
- Growing pains
- Indigestion

Warnings

Ask a doctor before use if you have:

- Symptoms that persist for more than 72 hours or worsen
- Gum swelling that increases
- A rash or fever develops
- Irritation, pain or redness persists or worsens
- Sensitive teeth may indicate a serious problem that may need prompt care by a dentist
- Severe indigestion symptoms warrant medical attention to rule out more serious issues.

If pregnant or breastfeeding, ask a health professional before use. Keep out of reach of children.

Directions

- Use as directed
- Take 30 minutes away from food.

Adults

- Acute dose: Spray into the mouth 4 times every 30 mins until symptoms subside, up to 8 times per day.
- Maintenance dose: Spray into mouth 4 times, 4 times per day.

Other Information

store below 86°F

Inactive Ingredients

Alcohol , Glycerin, water

Questions?www.schuesslertissuesalts.co or + 1-888-464-6775